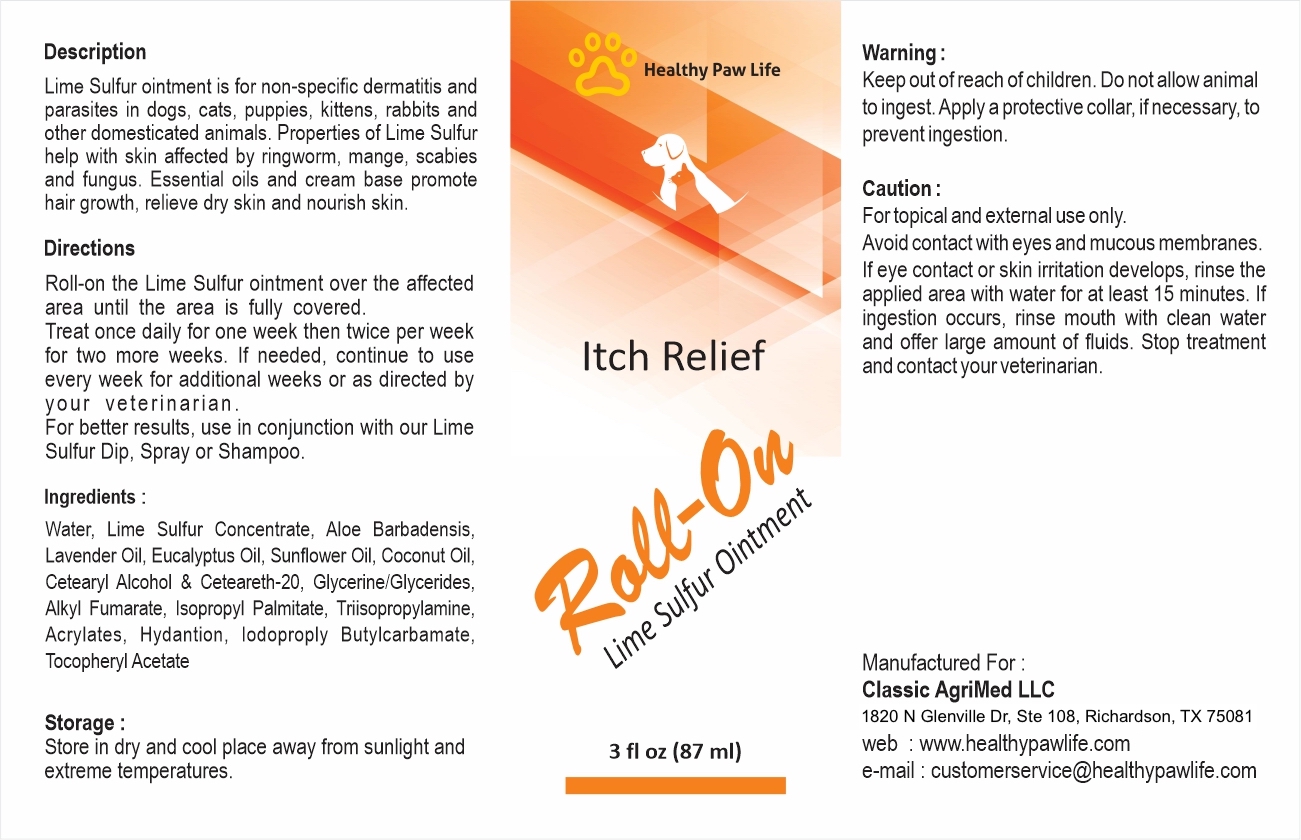 DRUG LABEL: HEALTHY PAW LIFE ROLLON
NDC: 86130-600 | Form: LOTION
Manufacturer: CLASSIC AGRIMED LLC
Category: animal | Type: OTC ANIMAL DRUG LABEL
Date: 20231118

ACTIVE INGREDIENTS: CALCIUM POLYSULFIDE 0.32 1/100 g

HEALTHY PAW LIFE LIME SULFUR ROLLON PET

Description:
Lime Sulfur ointment is for non-specific dermatitis and parasites in dogs, cats, puppies, kittens, rabbits and other domesticated animals. Properties of Lime Sulfur help with skin affected by ringworm, mange, scabies and fungus. Essential oils and cream base promote hair growth, relieve dry skin and nourish skin.

Warning:
Keep out of reach of children. Do not allow animal to ingest. Apply a protective collar, if necessary, to prevent ingestion.

Storage:
Store in dry and cool place away from sunlight and extreme temperatures.

Directions:
Roll-on the Lime Sulfur ointment over the affected area until the area is fully covered. Treat once daily for one week then twice per week for two more weeks. If needed, continue to use every week for additional weeks or as directed by your veterinarian. For better results, use in condjuction with our Lime Sulfur Dip, Spray or Shampoo.

Caution:
For topical and external use only. Avoid contact with eyes and mucous membranes. If eye contact or skin irritation develops, rinse the applied area with water for at least 15 minutes. If ingestion occurs, rinse the mouth with clean water and offer large amounts of fluids. Stop treatment and contact your veterinarian.

Ingredients:

Water, Lime Sulfur Concentrate, Aloe Barbadensis, Lavender Oil, Eucalyptus Oil, Sunflower Oil, Coconut Oil, Ceteraryl Alochol & Ceteareth-209, Glycerin/Glycerides, Alkyl Fumarate, Isopropyl Palmitate, Trissopropylamine, Acrylates, Hydantion, Idopropyl Butylcarbamate, Tocopheryl Acetate

Manufactured For: Classic Agrimed LLC